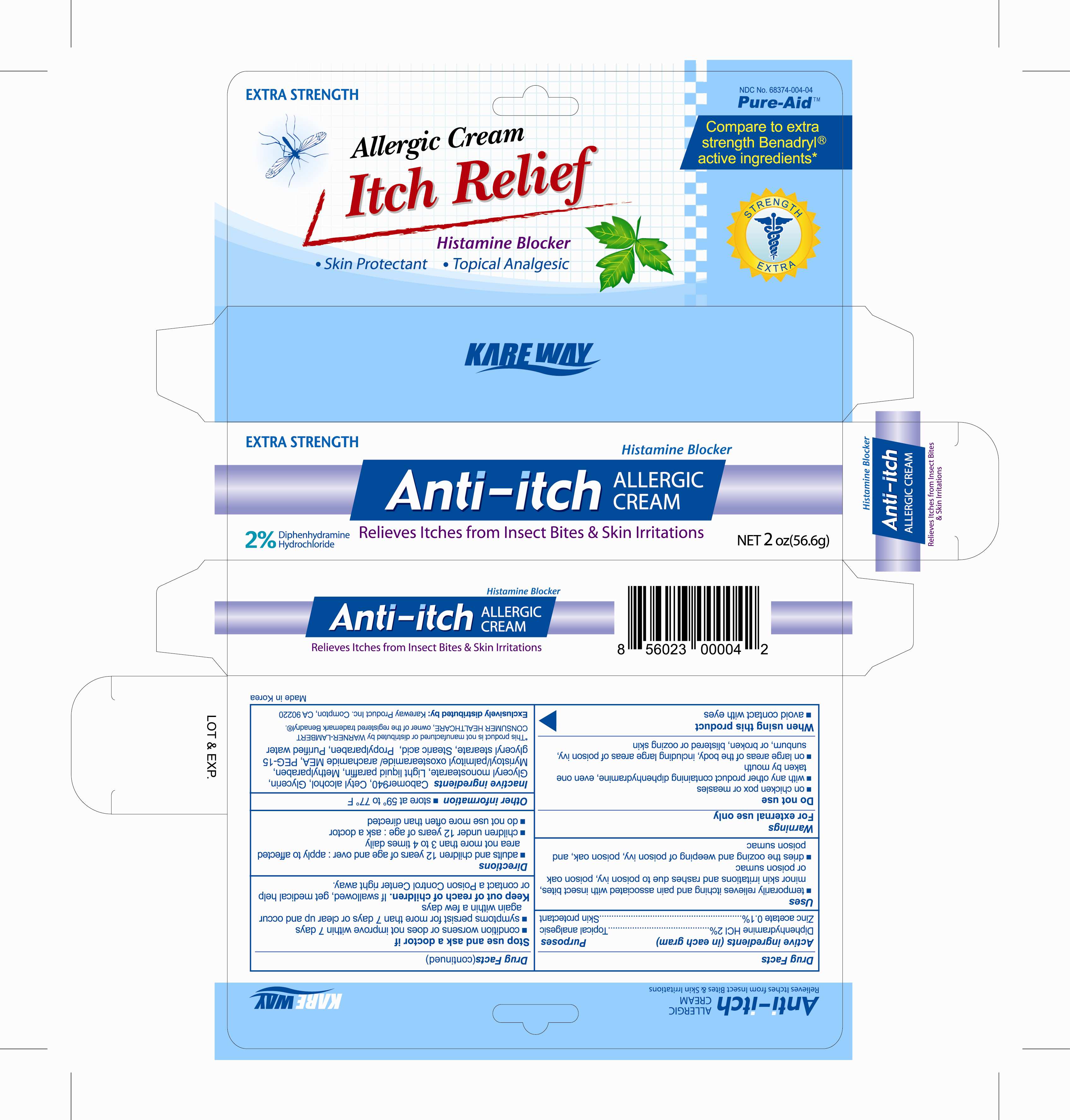 DRUG LABEL: Anti Itch Cream
NDC: 51141-0054 | Form: CREAM
Manufacturer: NeoPharm Co., Ltd.
Category: otc | Type: HUMAN OTC DRUG LABEL
Date: 20100829

ACTIVE INGREDIENTS: DIPHENHYDRAMINE HYDROCHLORIDE 2 g/100 g; ZINC ACETATE 0.1 g/100 g
INACTIVE INGREDIENTS: CARBOMER HOMOPOLYMER TYPE C; CETYL ALCOHOL; GLYCERIN; GLYCERYL MONOSTEARATE; PARAFFIN; METHYLPARABEN; GLYCERYL MONOSTEARATE; STEARIC ACID; PROPYLPARABEN; WATER

Drug Facts

Active ingredients (in each gram)

Diphenhydramine HCl 2%

Zinc acetate 0.1%

Purposes

Topical analgesic

Skin protectant

Uses

- temporarily relieves itching and pain associated with insect bites, minor skin irritations and rashes due to poison ivy, poison oak or poison sumac
- dries the oozing and weeping of poison ivy, poison oak, and poison sumac

Warnings

For external use only

Do not use

- on chicken pox or measles
- with any other product containing diphenhydramine, even one taken by mouth
- on large areas of the body, including large areas of poison ivy, sunburn, or broken, blistered or oozing skin

Stop use and ask a doctor if

- condition worsens or does not improve within 7 days
- symptoms persist for more than 7 days or clear up and occur again within a few days

Keep out of reach of children

If swallowed, get medical help or contact a Poison Control Center right away

Directions

- adults and children 12 years of age and over: apply to affected area not more than 3 to 4 times daily
- children under 12 years of age: ask a doctor
- do not use more often than directed

Other information

- store at 59° to 77°F

Inactive ingredients

Carbomer 940, Cetyl alcohol, Glycerin, Glyceryl monostearate, Light liquid paraffin, Methylparaben, Myristoyl/palmitoyl oxostearamide/ arachamide MEA, PEG-15 glyceryl stearate, Stearic acid, Propylparaben, Purified water

Package label

Anti-Itch Cream